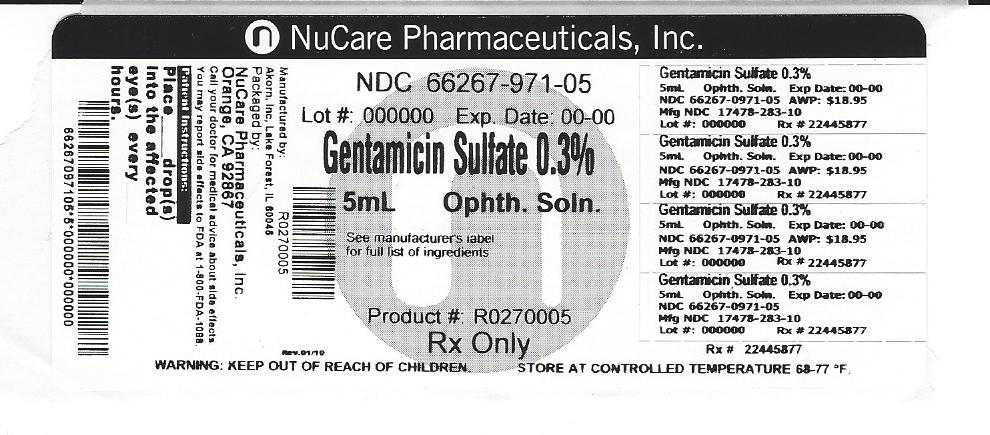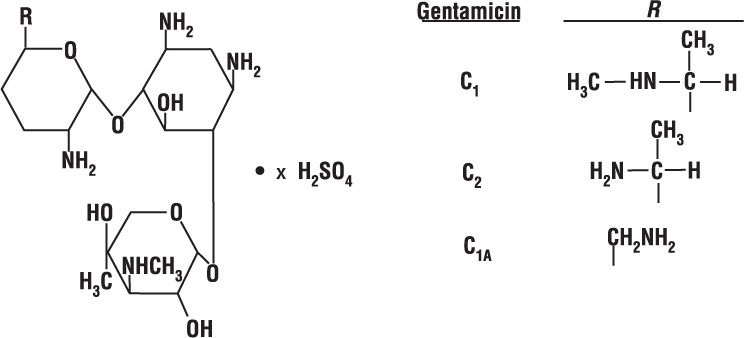 DRUG LABEL: Gentamicin Sulfate
NDC: 66267-971 | Form: SOLUTION/ DROPS
Manufacturer: NuCare Pharmaceuticals, Inc.
Category: prescription | Type: HUMAN PRESCRIPTION DRUG LABEL
Date: 20240814

ACTIVE INGREDIENTS: GENTAMICIN SULFATE 3 mg/1 mL
INACTIVE INGREDIENTS: SODIUM PHOSPHATE, MONOBASIC; SODIUM PHOSPHATE, DIBASIC, ANHYDROUS; SODIUM CHLORIDE; BENZALKONIUM CHLORIDE

Gentamicin Sulfate Ophthalmic Solution USP, 0.3%

Sterile

Rx only

DESCRIPTION

Gentamicin sulfate is a water-soluble antibiotic of the aminoglycoside group.

Gentamicin Sulfate Ophthalmic Solution is a sterile, aqueous solution for ophthalmic use.

Each mL contains:
Active: Gentamicin Sulfate USP (equivalent to 3 mg gentamicin base)
Preservative: Benzalkonium Chloride
Inactives: Disodium Phosphate, Monosodium Phosphate, and Sodium Chloride. The pH range is from 6.8 to 7.3.

Gentamicin is obtained from cultures of Micromonospora purpurea. It is a mixture of the sulfate salts of gentamicin C1, C2, and C1A. All three components appear to have similar antimicrobial activities. Gentamicin sulfate occurs as a white powder and is soluble in water and insoluble in alcohol. The structural formula is as follows:

CLINICAL PHARMACOLOGY

Microbiology

Gentamicin sulfate is active in vitro against many strains of the following microorganisms:

- Staphylococcus aureus, Staphylococcus epidermidis, Streptococcus pyogenes, Streptococcus pneumoniae, Enterobacter aerogenes, Escherichia coli, Haemophilus influenzae, Klebsiella pneumoniae, Neisseria gonorrhoeae, Pseudomonas aeruginosa, and Serratia marcescens.

INDICATIONS AND USAGE

Gentamicin Sulfate Sterile Ophthalmic Solution is indicated in the topical treatment of ocular bacterial infections, including conjunctivitis, keratitis, keratoconjunctivitis, corneal ulcers, blepharitis, blepharoconjunctivitis, acute meibomianitis, and dacryocystitis caused by susceptible strains of the following microorganisms:

- Staphylococcus aureus, Staphylococcus epidermidis, Streptococcus pyogenes, Streptococcus pneumoniae, Enterobacter aerogenes, Escherichia coli, Haemophilus influenzae, Klebsiella pneumoniae, Neisseria gonorrhoeae, Pseudomonas aeruginosa, and Serratia marcescens.

CONTRAINDICATIONS

Gentamicin Sulfate Sterile Ophthalmic Solution is contraindicated in patients with known hypersensitivity to any of the components.

WARNINGS

NOT FOR INJECTION INTO THE EYE. Gentamicin Sulfate Ophthalmic Solution is not for injection. It should never be injected subconjunctivally, nor should it be directly introduced into the anterior chamber of the eye.

PRECAUTIONS

General

Prolonged use of topical antibiotics may give rise to overgrowth of nonsusceptible organisms including fungi. Bacterial resistance to gentamicin may also develop. If purulent discharge, inflammation or pain becomes aggravated, the patient should discontinue use of the medication and consult a physician.

If irritation or hypersensitivity to any component of the drug develops, the patient should discontinue use of this preparation and appropriate therapy should be instituted.

Information for patients

To avoid contamination, do not touch tip of container to the eye, eyelid or any surface.

Carcinogenesis, Mutagenesis, Impairment of Fertility

There are no published carcinogenicity or impairment of fertility studies on gentamicin. Aminoglycoside antibiotics have been found to be non mutagenic.

Pregnancy

Pregnancy Category C

Gentamicin has been shown to depress body weights, kidney weights and median glomerular counts in newborn rats when administered systemically to pregnant rats in daily doses approximately 500 times the maximum recommended ophthalmic human dose. There are no adequate and well-controlled studies in pregnant women. Gentamicin should be used during pregnancy only if the potential benefit justifies the potential risk to the fetus.

Pediatric Use

Safety and effectiveness in neonates have not been established.

ADVERSE REACTIONS

Bacterial and fungal corneal ulcers have developed during treatment with gentamicin ophthalmic preparations.

The most frequently reported adverse reactions are ocular burning and irritation upon drug instillation, non-specific conjunctivitis, conjunctival epithelial defects and conjunctival hyperemia.

Other adverse reactions which have occurred rarely are allergic reactions, thrombocytopenic purpura and hallucinations.

DOSAGE AND ADMINISTRATION

Gentamicin Sulfate sterile ophthalmic solution; Instill one or two drops into the affected eye(s) every four hours. In severe infections, dosage may be increased to as much as two drops once every hour.

HOW SUPPLIED

Gentamicin Sulfate ophthalmic solution - Sterile, 5-mL plastic dropper bottle, box of one. (NDC 66267-971-05)

STORAGE AND HANDLING

STORAGE: Store at 20° to 25°C (68° to 77°F) [see USP Controlled Room Temperature].

Avoid exposure to excessive heat.

Akorn

Manufactured by: Akorn, Inc.
Lake Forest, IL 60045

GK00N

Rev. 11/11